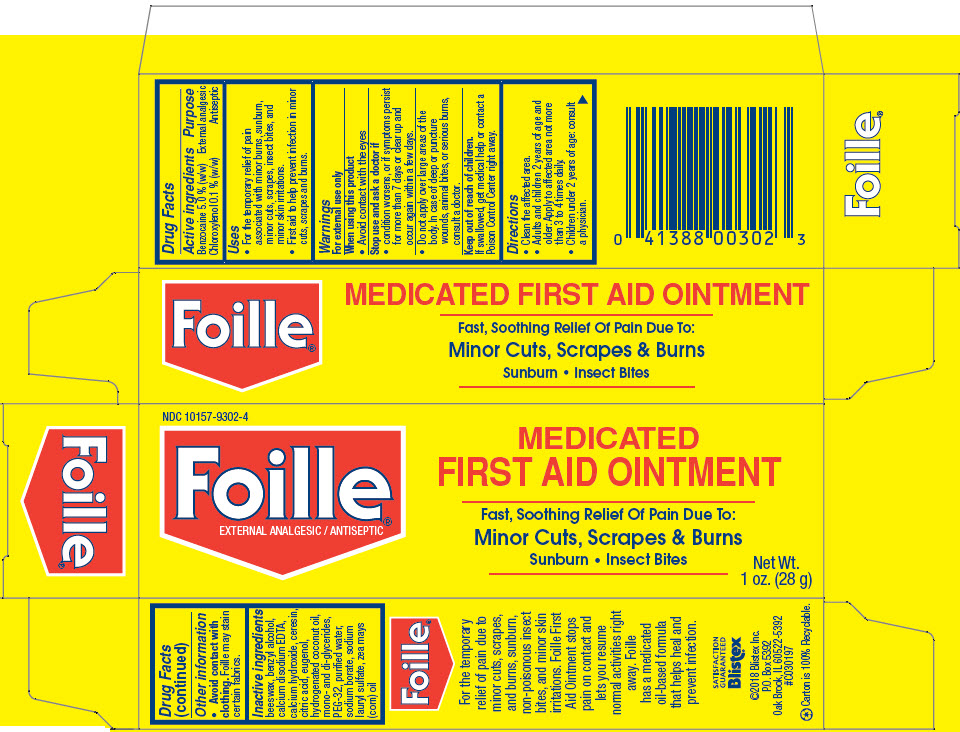 DRUG LABEL: Blistex 
NDC: 10157-9302 | Form: OINTMENT
Manufacturer: Blistex Inc.
Category: otc | Type: HUMAN OTC DRUG LABEL
Date: 20241211

ACTIVE INGREDIENTS: Benzocaine 5 g/100 g; Chloroxylenol 0.1 g/100 g
INACTIVE INGREDIENTS: corn oil; HYDROGENATED COCONUT OIL; yellow wax; POLYETHYLENE GLYCOL 1600; water; benzyl alcohol; GLYCERYL MONO- AND DIPALMITOSTEARATE; ceresin; sodium borate; calcium hydroxide; edetate calcium disodium anhydrous; eugenol; sodium lauryl sulfate

Blistex®
Foille® Medicated First Aid Ointment

Drug Facts

ACTIVE INGREDIENT

Active ingredients | Purpose
Benzocaine 5.0 % (w/w) | External analgesic
Chloroxylenol 0.1 % (w/w) | Antiseptic

Uses

- For the temporary relief of pain associated with minor burns, sunburn, minor cuts, scrapes, insect bites, and minor skin irritations.
- First aid to help prevent infection in minor cuts, scrapes and burns.

Warnings

For external use only

When using this product

- Avoid contact with the eyes

Stop use and ask a doctor if

- condition worsens, or if symptoms persist for more than 7 days or clear up and occur again within a few days.

DO NOT USE

- Do not apply over large areas of the body. In case of deep or puncture wounds, animal bites, or serious burns, consult a doctor.

Keep out of reach of children.

If swallowed, get medical help or contact a Poison Control Center right away.

Directions

- Clean the affected area.
- Adults and children 2 years of age and older: Apply to affected area not more than 3 to 4 times daily.
- Children under 2 years of age: consult a physician.

Other information

- Avoid contact with clothing. Foille may stain certain fabrics.

Inactive ingredients

beeswax, benzyl alcohol, calcium disodium EDTA, calcium hydroxide, ceresin, citric acid, eugenol, hydrogenated coconut oil, mono- and di-glycerides, PEG-32, purified water, sodium borate, sodium lauryl sulfate, zea mays (corn) oil

PRINCIPAL DISPLAY PANEL - 28 g Tube Carton

NDC 10157-9302-4

Foille®
EXTERNAL ANALGESIC / ANTISEPTIC

MEDICATED
FIRST AID OINTMENT

Fast, Soothing Relief Of Pain Due To:
Minor Cuts, Scrapes & Burns
Sunburn • Insect Bites

Net Wt.
1 oz. (28 g)